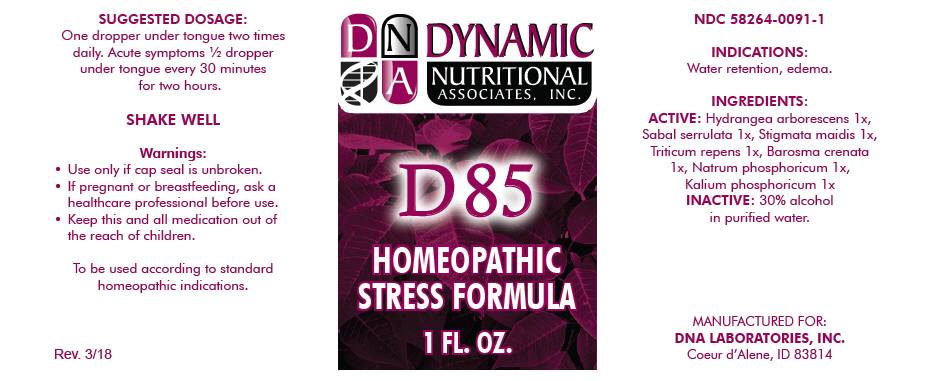 DRUG LABEL: D-85
NDC: 58264-0091 | Form: SOLUTION
Manufacturer: DNA Labs, Inc.
Category: homeopathic | Type: HUMAN OTC DRUG LABEL
Date: 20250113

ACTIVE INGREDIENTS: HYDRANGEA ARBORESCENS ROOT 1 [hp_X]/1 mL; SAW PALMETTO 1 [hp_X]/1 mL; CORN SILK 1 [hp_X]/1 mL; ELYMUS REPENS ROOT 1 [hp_X]/1 mL; AGATHOSMA CRENULATA LEAF 1 [hp_X]/1 mL; SODIUM PHOSPHATE, DIBASIC, HEPTAHYDRATE 1 [hp_X]/1 mL; DIBASIC POTASSIUM PHOSPHATE 1 [hp_X]/1 mL
INACTIVE INGREDIENTS: ALCOHOL; WATER

D-85

NDC 58264-0091-1

INDICATIONS

PURPOSE

Water retention, edema.

INGREDIENTS

ACTIVE

Hydrangea arborescens 1x, Sabal serrulata 1x, Stigmata maidis 1x, Triticum repens 1x, Barosma crenata 1x, Natrum phosphoricum 1x, Kalium phosphoricum 1x

INACTIVE

30% alcohol in purified water.

SUGGESTED DOSAGE

One dropper under tongue two times daily. Acute symptoms ½ dropper under tongue every 30 minutes for two hours.

STORAGE AND HANDLING

SHAKE WELL

Warnings

- Use only if cap seal is unbroken.

PREGNANCY OR BREAST FEEDING

- If pregnant or breastfeeding, ask a healthcare professional before use.

KEEP OUT OF REACH OF CHILDREN

- Keep this and all medication out of the reach of children.

To be used according to standard homeopathic indications.

PRINCIPAL DISPLAY PANEL - 1 FL. OZ. Bottle Label

DYNAMIC
NUTRITIONAL
ASSOCIATES, INC.

D 85

HOMEOPATHIC
STRESS FORMULA

1 FL. OZ.